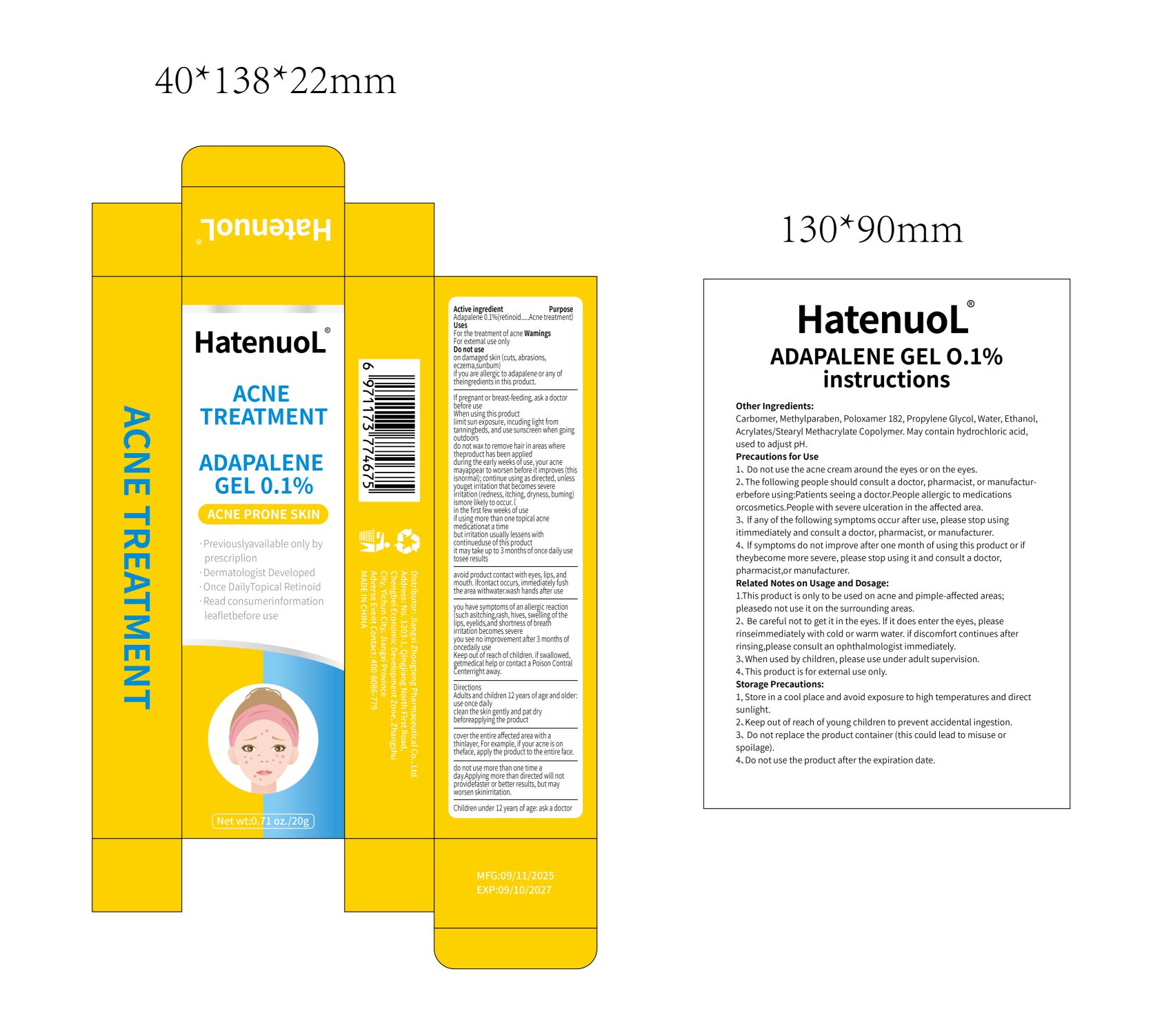 DRUG LABEL: ACNE TREATMENT
NDC: 87240-396 | Form: GEL
Manufacturer: Jiangxi Zhongteng Pharmaceutical Co., Ltd
Category: homeopathic | Type: HUMAN OTC DRUG LABEL
Date: 20251120

ACTIVE INGREDIENTS: ADAPALENE 1 g/1 1
INACTIVE INGREDIENTS: CARBOMER 934; ALUMINUM DICHLOROHYDREX PROPYLENE GLYCOL; POLOXAMER 182; METHYLPARABEN; WATER

ACTIVE INGREDIENT

Adapalene

PURPOSE

For the treatment of acne wamings for extemal use only

keep out of reach of children section

INDICATIONS AND USAGE

For the treatment of acne wamings for extemal use only

Once a day

WARNINGS

keep out of children

DOSAGE AND ADMINISTRATION

Once a day

INACTIVE INGREDIENT

Carbomer,Methylparaben,Propylene Glycol,Water